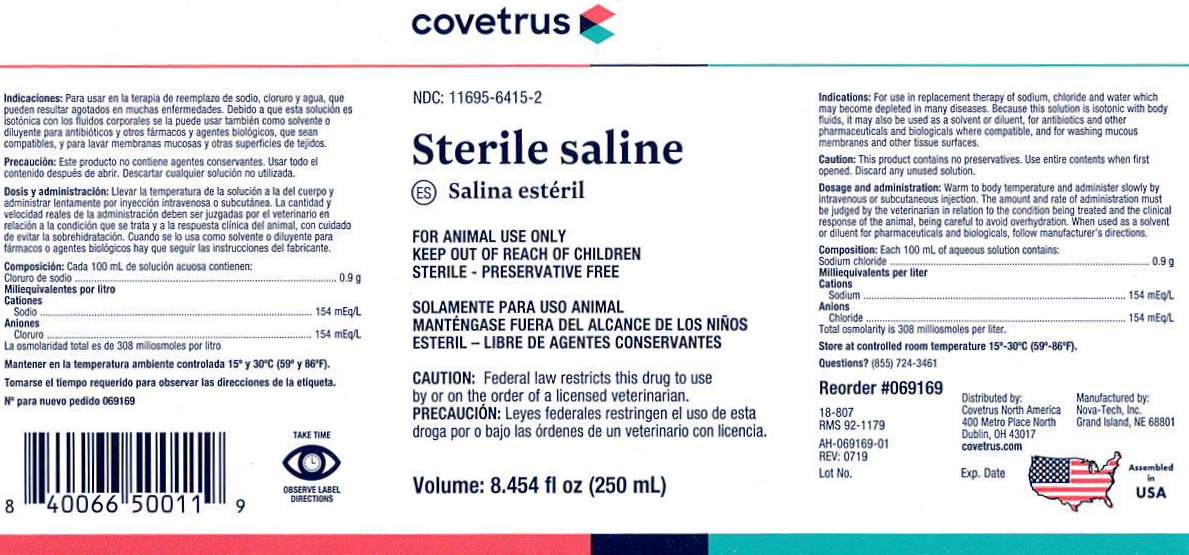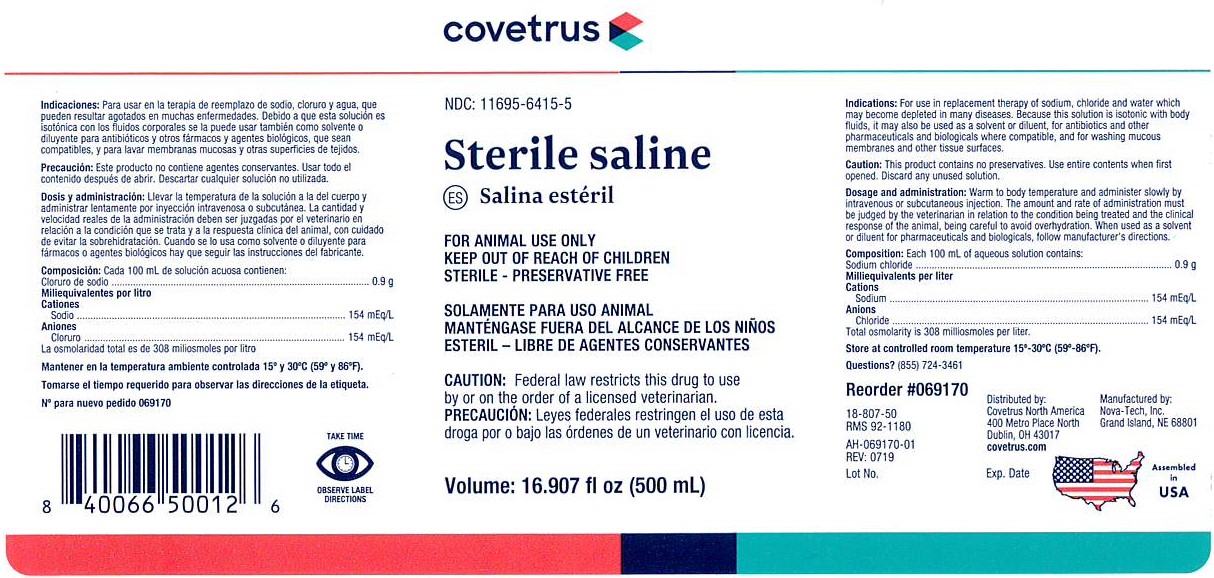 DRUG LABEL: Sterile saline
NDC: 11695-6415 | Form: INJECTION, SOLUTION
Manufacturer: Covetrus
Category: animal | Type: PRESCRIPTION ANIMAL DRUG LABEL
Date: 20191202

ACTIVE INGREDIENTS: Sodium Chloride 0.9 g/100 mL

Sterile Saline

INDICATIONS:

For use in replacement therapy of sodium, chloride and water which may become depleted in many diseases. Because this solution is isotonic with body fluids, it may also be used as a solvent or diluent for antibiotics and other pharmaceuticals and biologicals where compatible, and for washing mucous membranes and other tissue surfaces.

CAUTION:

This product contains no preservatives. Use entire contents when first opened. Discard any unused solution.

DOSAGE AND ADMINISTRATION:

Warm to body temperature and administer slowly by intravenous or subcutaneous injection. The amount and rate of administration must be judged by the veterinarian in relation to the condition being treated and the clinical response of the animal, being careful to avoid overhydration. When used as a solvent or diluent for pharmaceuticals and biologicals, follow manufacturer's directions.

VETERINARY INDICATIONS

FOR ANIMAL USE ONLY

KEEP OUT OF REACH OF CHILDREN

CAUTION:

Federal law restricts this drug to use by or on the order of a licensed veterinarian.

COMPOSITION:

Each 100 mL of aqueous solution contains:

Sodium chloride ....................................... 0.9 g

Milliequivalents per liter

Cations

Sodium ....................................... 154 mEq/L

Anions

Chloride ..................................... 154 mEq/L

Total osmolarity is 308 milliosmoles per liter.

STORAGE AND HANDLING

Store at controlled room temperature 15°C - 30°C (59°F - 86°F).

PRECAUTIONS

TAKE TIME OBSERVE LABEL DIRECTIONS

INFORMATION FOR OWNERS/CAREGIVERS

Questions? (855) 724-3461

Reorder #069169

18-807

RMS 92-1179

AH-069169-01

REV: 0719

NDC: 11695-6415-2

Sterilie - Preservative Free

Volume: 8.454 fl oz (250 mL)

Manufactured by:

Nova-Tech, Inc.

Grand Island, NE 68801

Distributed by:

Covetrus North America

400 Metro Place North

Dublin, OH 43017

covetrus.com

Lot No.

Exp. Date

Assembled in USA